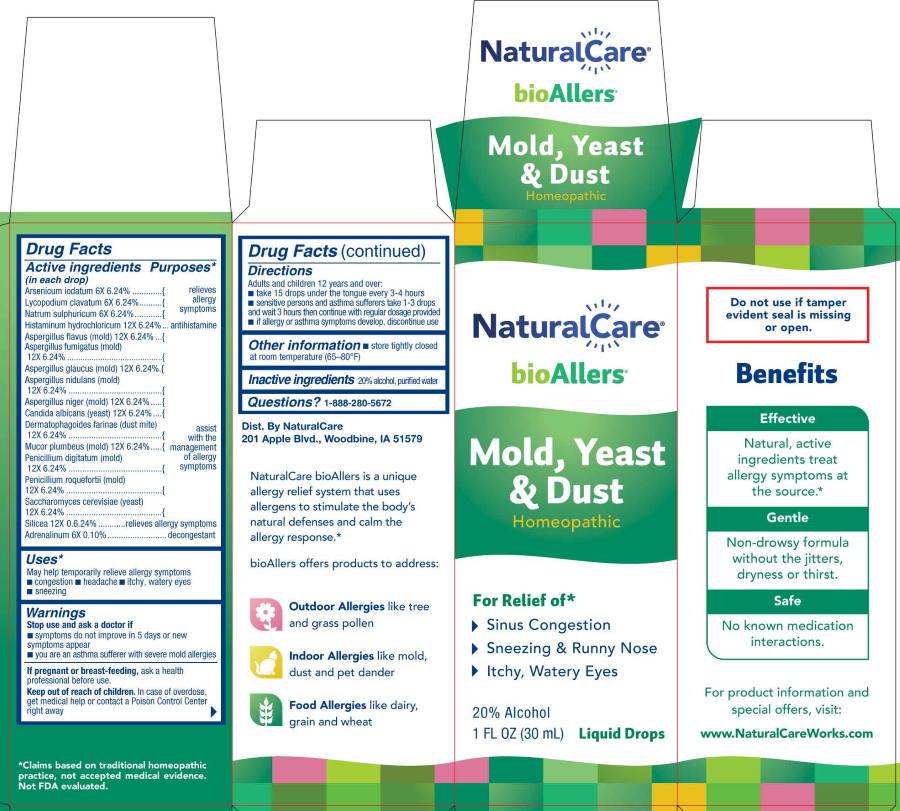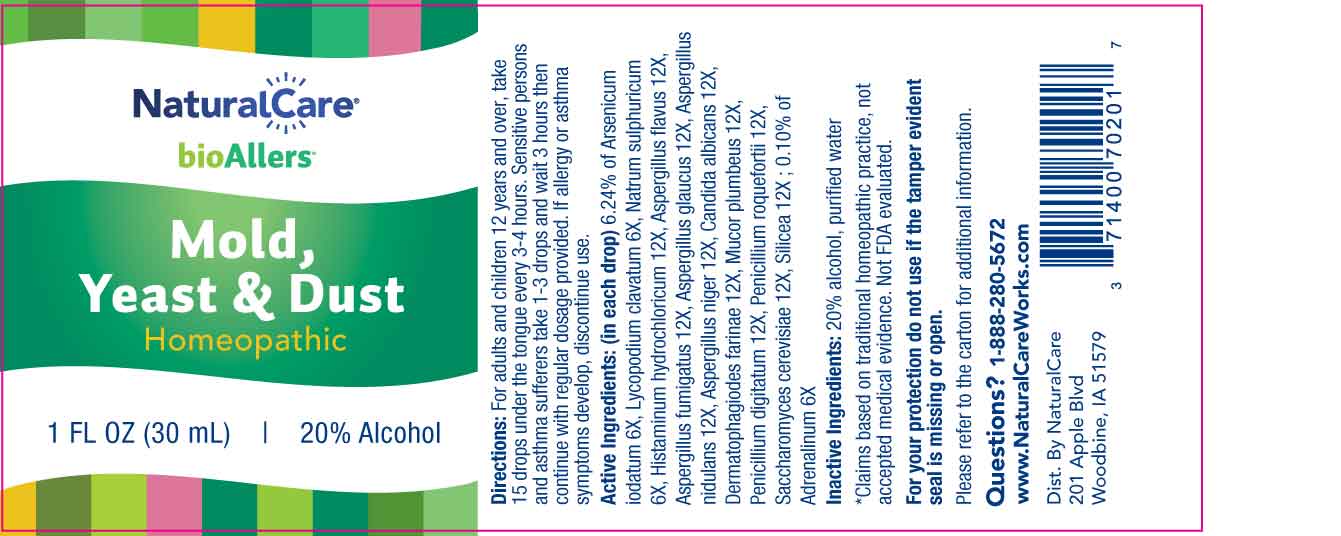 DRUG LABEL: Mold, Yeast and Dust
NDC: 70163-0019 | Form: LIQUID
Manufacturer: NaturalCare
Category: homeopathic | Type: HUMAN OTC DRUG LABEL
Date: 20260209

ACTIVE INGREDIENTS: EPINEPHRINE 6 [hp_X]/1 mL; ARSENIC TRIIODIDE 6 [hp_X]/1 mL; ASPERGILLUS FLAVUS 12 [hp_X]/1 mL; ASPERGILLUS FUMIGATUS 12 [hp_Q]/1 mL; EUROTIUM HERBARIORUM 12 [hp_X]/1 mL; ASPERGILLUS NIDULANS 12 [hp_X]/1 mL; ASPERGILLUS NIGER VAR. NIGER 12 [hp_X]/1 mL; CANDIDA ALBICANS 12 [hp_X]/1 mL; DERMATOPHAGOIDES FARINAE 12 [hp_X]/1 mL; HISTAMINE DIHYDROCHLORIDE 12 [hp_X]/1 mL; LYCOPODIUM CLAVATUM SPORE 6 [hp_X]/1 mL; MUCOR PLUMBEUS 12 [hp_X]/1 mL; SODIUM SULFATE 6 [hp_X]/1 mL; PENICILLIUM DIGITATUM 12 [hp_X]/1 mL; PENICILLIUM ROQUEFORTI 12 [hp_X]/1 mL; SACCHAROMYCES CEREVISIAE 12 [hp_X]/1 mL; SILICON DIOXIDE 12 [hp_X]/1 mL
INACTIVE INGREDIENTS: WATER; ALCOHOL

DRUG FACTS:

ACTIVE INGREDIENT:

(in each drop) 6.24% of Arsenicum Iodatum 6X, Lycopodium Clavatum 6X, Natrum Sulphuricum 6X, Histaminum Hydrochloricum 12X, Aspergillus Flavus 12X, Aspergillus Fumigatus 12X, Aspergillus Glaucus 12X, Aspergillus Nidulans 12X, Aspergillus Niger 12X, Candida Albicans 12X, Dermatophagoides Farinae 12X, Mucor Plumbeus 12X, Penicillium Digitatum 12X, Penicillium Roquefortii 12X, Saccharomyces Cerevisiae 12X, Silicea 12X; 0.10% of Adrenalinum 6X.

PURPOSE:

Arsenicum Iodatum – relieves allergy symptoms, Lycopodium Clavatum - relieves allergy symptoms, Natrum Sulphuricum - relieves allergy symptoms, Histaminum Hydrochloricum - antihistamine, Aspergillus Flavus – assist with the management of allergy symptoms, Aspergillus Fumigatus - assist with the management of allergy symptoms, Aspergillus Glaucus - assist with the management of allergy symptoms, Aspergillus Nidulans - assist with the management of allergy symptoms, Aspergillus Niger - assist with the management of allergy symptoms, Candida Albicans - assist with the management of allergy symptoms, Dermatophagoides Farinae - assist with the management of allergy symptoms, Mucor Plumbeus - assist with the management of allergy symptoms, Penicillium Digitatum - assist with the management of allergy symptoms, Penicillium Roquefortii - assist with the management of allergy symptoms, Saccharomyces Cerevisiae - assist with the management of allergy symptoms, Silicea – relieves allergy symptoms, Adrenalinum - decongestant*

*Claims based on traditional homeopathic practice, not accepted medical evidence. Not FDA evaluated.

USES:

May help temporarily relieve allergy symptoms

■ congestion ■ headache ■ itchy, watery eyes ■ sneezing

*Claims based on traditional homeopathic practice, not accepted medical evidence. Not FDA evaluated.

WARNINGS:

Stop use and ask a doctor if

■ symptoms do not improve in 5 days or new symptoms appear

■ you are an asthma sufferer with severe mold allergies

If pregnant or breast-feeding, ask a health professional before use.

Keep out of reach of children. In case of overdose, get medical help or contact a Poison Control Center right away.

Do not use if tamper evident seal is missing or open.

■ Store tightly closed at room temperature (65-80ºF)

KEEP OUT OF REACH OF CHILDREN:

In case of overdose, get medical help or contact a Poison Control Center right away.

DIRECTIONS:

Adults and children 12 years and over:

■ take 15 drops under the tongue every 3-4 hours

■ sensitive persons and asthma sufferers take 1-3 drops and wait 3 hours then continue with regular dosage provided

■ if allergy or asthma symptoms develop, discontinue use

INACTIVE INGREDIENTS:

20% alcohol, purified water

QUESTIONS:

Dist. By NaturalCare

201 Apple Blvd.

Woodbine, IA 51579

www.NaturalCareWorks.com

1-888-280-5672

PACKAGE LABEL DISPLAY:

NaturalCare

bioAllers

Mold, Yeast & Dust

Homeopathic

1 FL OZ (30 mL)